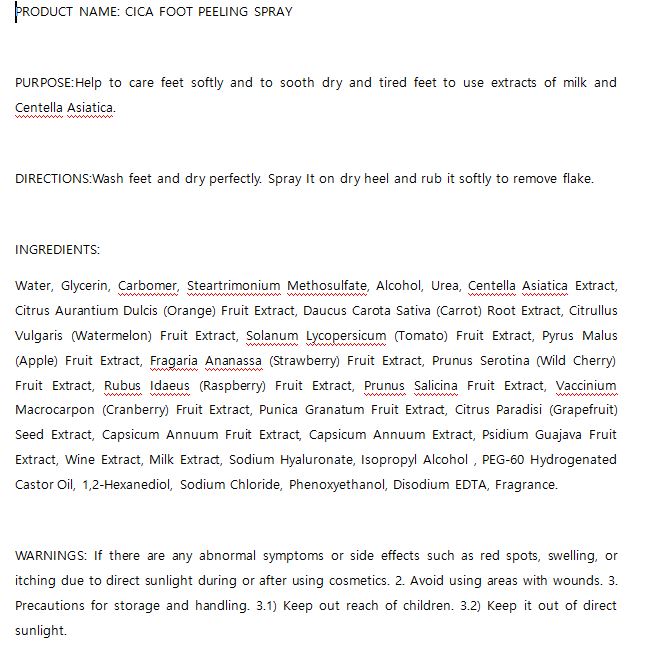 DRUG LABEL: W.SKIN CICA FOOT PEELING
NDC: 74997-0018 | Form: LIQUID
Manufacturer: J&J COMPANY
Category: otc | Type: HUMAN OTC DRUG LABEL
Date: 20210507

ACTIVE INGREDIENTS: CENTELLA ASIATICA 0.01 g/100 mL; UREA 0.2 g/100 mL
INACTIVE INGREDIENTS: GLYCERIN; WATER

J&J COMPANY - STOP-AGING PEPTIDE TONER

ACTIVE INGREDIENT

Centella Asiatica Extract 0.01

Urea 0.2

INACTIVE INGREDIENT

Water, Glycerin, Carbomer, Steartrimonium Methosulfate, Alcohol, Urea, Centella Asiatica Extract, Citrus Aurantium Dulcis (Orange) Fruit Extract, Daucus Carota Sativa (Carrot) Root Extract, Citrullus Vulgaris (Watermelon) Fruit Extract, Solanum Lycopersicum (Tomato) Fruit Extract, Pyrus Malus (Apple) Fruit Extract, Fragaria Ananassa (Strawberry) Fruit Extract, Prunus Serotina (Wild Cherry) Fruit Extract, Rubus Idaeus (Raspberry) Fruit Extract, Prunus Salicina Fruit Extract, Vaccinium Macrocarpon (Cranberry) Fruit Extract, Punica Granatum Fruit Extract, Citrus Paradisi (Grapefruit) Seed Extract, Capsicum Annuum Fruit Extract, Capsicum Annuum Extract, Psidium Guajava Fruit Extract, Wine Extract, Milk Extract, Sodium Hyaluronate, Isopropyl Alcohol , PEG-60 Hydrogenated Castor Oil, 1,2-Hexanediol, Sodium Chloride, Phenoxyethanol, Disodium EDTA, Fragrance

PURPOSE

Help to care feet softly and to sooth dry and tired feet to use extracts of milk and Centella Asiatica.

keep out of reach of the children

INDICATIONS AND USAGE

Wash feet and dry perfectly. Spray It on dry heel and rub it softly to remove flake

WARNINGS

If there are any abnormal symptoms or side effects such as red spots, swelling, or itching due to direct sunlight during or after using cosmetics. 2. Avoid using areas with wounds. 3. Precautions for storage and handling. 3.1) Keep out reach of children. 3.2) Keep it out of direct sunlight.

DOSAGE AND ADMINISTRATION

for external use only